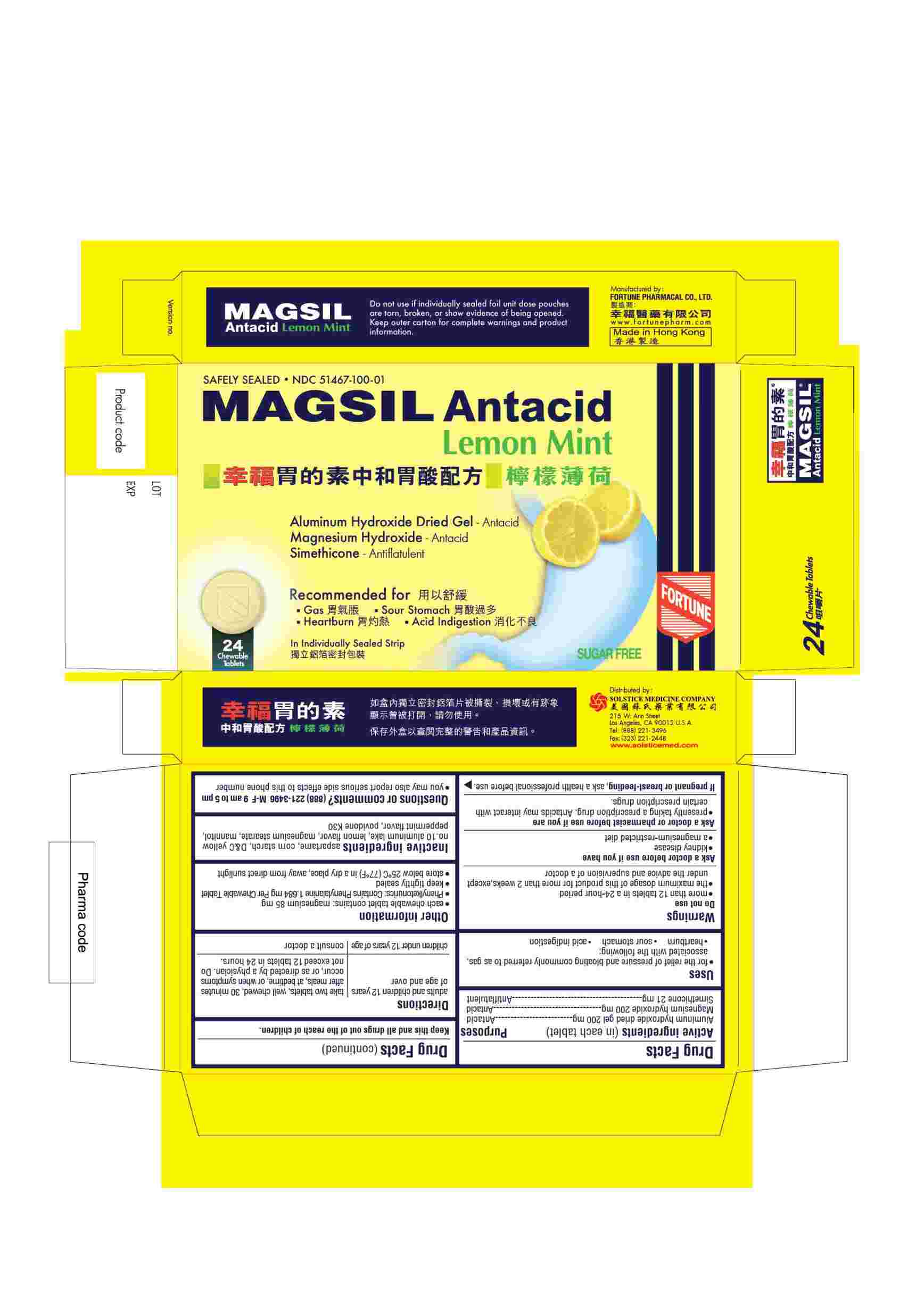 DRUG LABEL: MAGSIL ANTACID (LEMON MINT)
NDC: 51467-100 | Form: TABLET, CHEWABLE
Manufacturer: FORTUNE PHARMACAL COMPANY LIMITED
Category: otc | Type: HUMAN OTC DRUG LABEL
Date: 20251113

ACTIVE INGREDIENTS: ALUMINUM HYDROXIDE 200 mg/1 1; MAGNESIUM HYDROXIDE 200 mg/1 1; DIMETHICONE 21 mg/1 1
INACTIVE INGREDIENTS: ASPARTAME; STARCH, CORN; D&C YELLOW NO. 10; MAGNESIUM STEARATE; MANNITOL; POVIDONE K30

DRUG FACTS

Active ingredients(in each tablet)
Aluminum hydroxide dried gel 200 mg
Magnesium hydroxide 200 mg
Simethicone 21 mg

Purpose
Antacid
Antacid
Antiflatulent

Uses
■ for the relief of pressure and bloating commonly referred to as gas, associated with the following:
■ heartburn
■ sour stomach
■ acid indigestion

Warnings
Do not use
■ more than 12 tablets in a 24-hour period
■ the maximum dosage of this product for more than 2 weeks, except under the advice and supervision of a doctor

Ask a doctor before use if you have
■ kidney disease
■ a magnesium-restricted diet

Ask a doctor or pharmacist before use if you are
■ presently taking a prescription drug. Antacids may interact with certain prescription drugs.

PREGNANCY OR BREAST FEEDING

If pregnant or breast-feeding,ask a health professional before use.

KEEP OUT OF REACH OF CHILDREN

Keep this and all drugs out of the reach of children.

Directions
■ adults and children 12 years of age or older: take two tablets, well chewed, 30 minutes after meals, at bedtime, or when symptoms occur, or as directed by a physician. Do not exceed 12 tablets in 24 hours.
■ children under 12 years of age: consult a doctor

Other information
■ each chewable tablet contains: 85 mg of magnesium
■ Phenylketonurics: Contains Phenylalanine 1.684 mg Per Chewable Tablet
■ keep tightly sealed
■ store below 25 C (77 F) in a dry place, away from direct sunlight

Inactive ingredients
aspartame, corn starch, D&C yellow no. 10 aluminum lake, lemon flavor, magnesium stearate, mannitol, peppermint flavor, povidone K30

Questions or comments?(888) 221-3496 M-F 9 am to 5 pm
■ you may also report serious side effects to this phone number

PACKAGE LABEL

MAGSIL Antacid

Lemon Mint

Safely Sealed

NDC 51467-100-01

Aluminum Hydroxide Dried Gel - Antacid
Magnesium Hydroxide - Antacid
Simethicone - Antiflatulent

Recommended for
■ Gas
■ Sour Stomach
■ Heartburn
■ Acid Indigestion

24 Tablets

In Individually Sealed Strip

Sugar Free